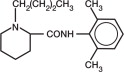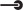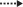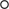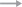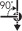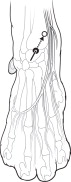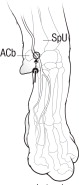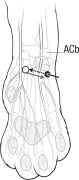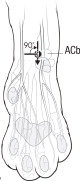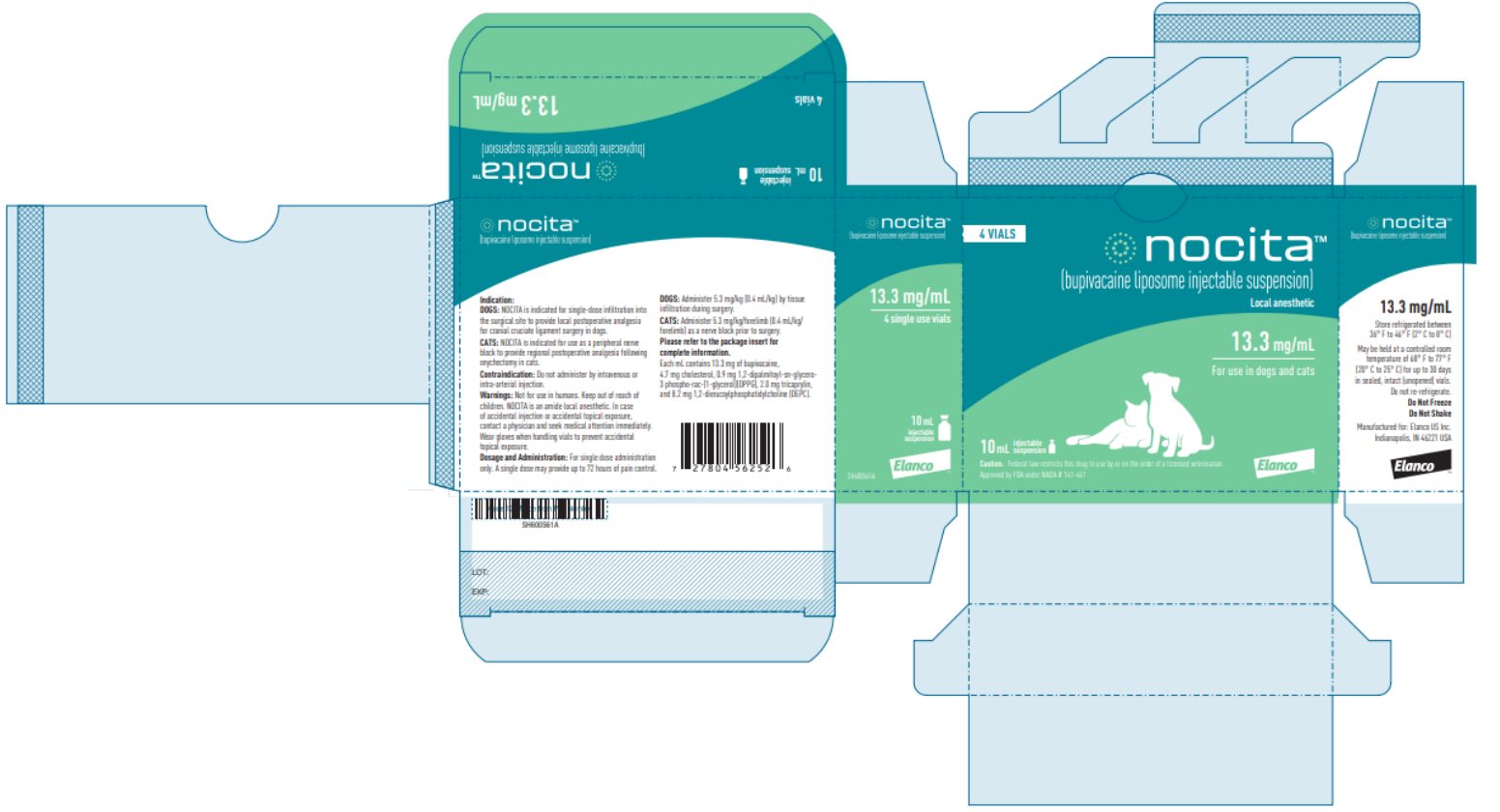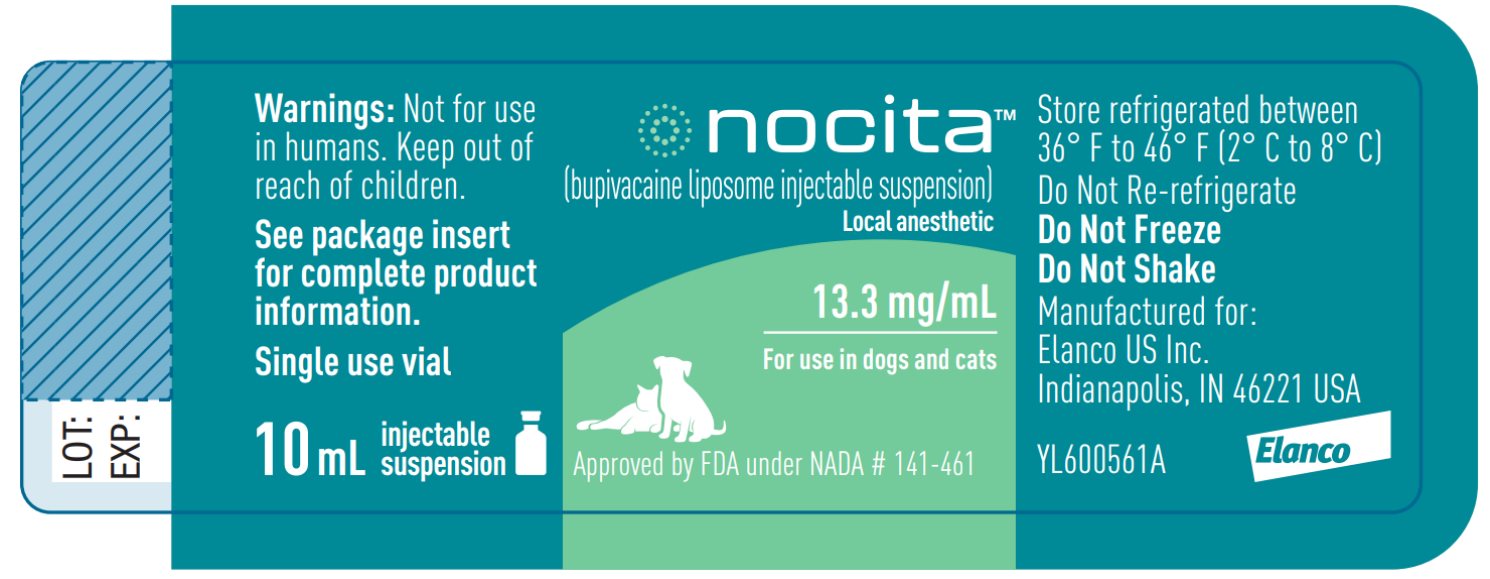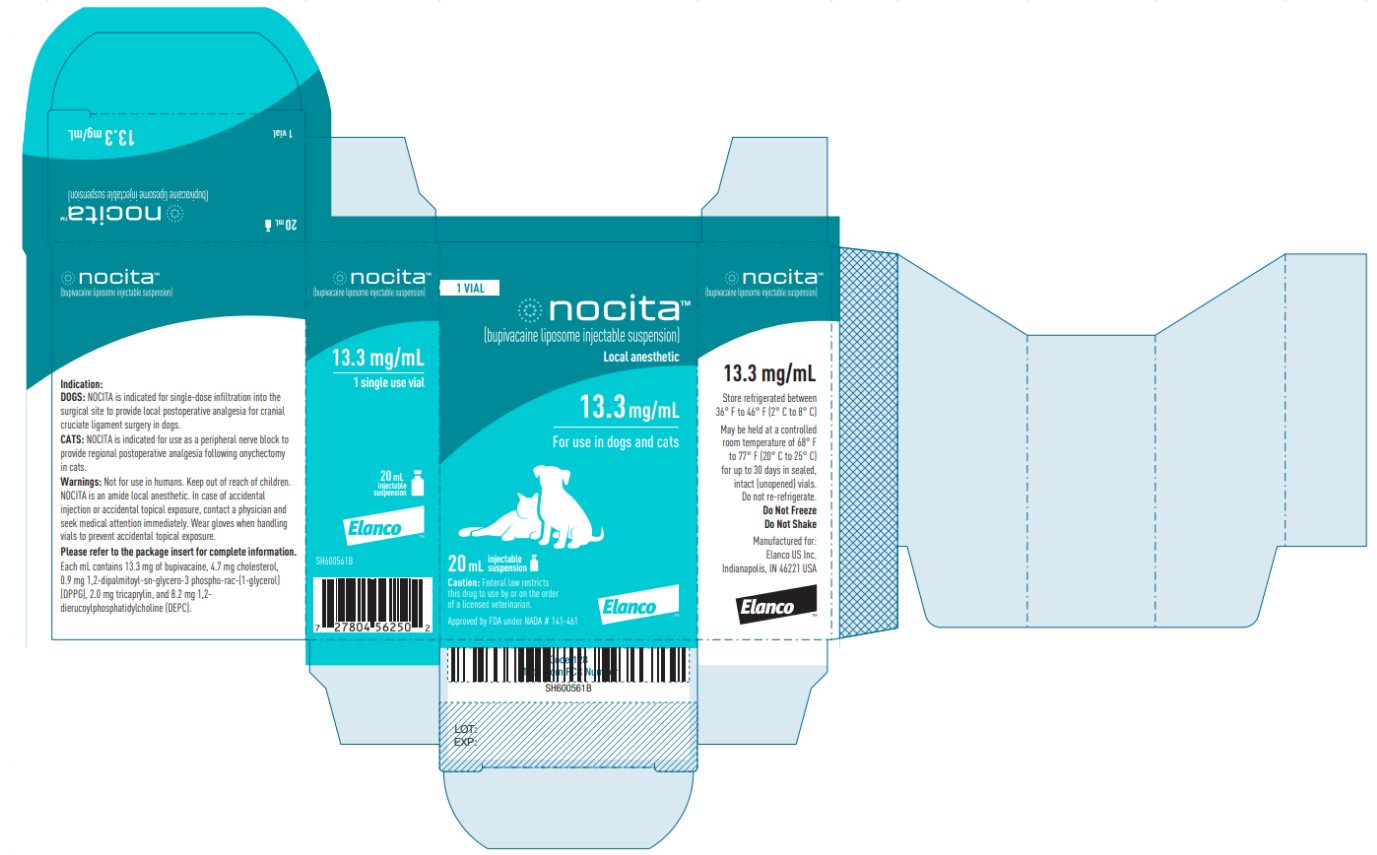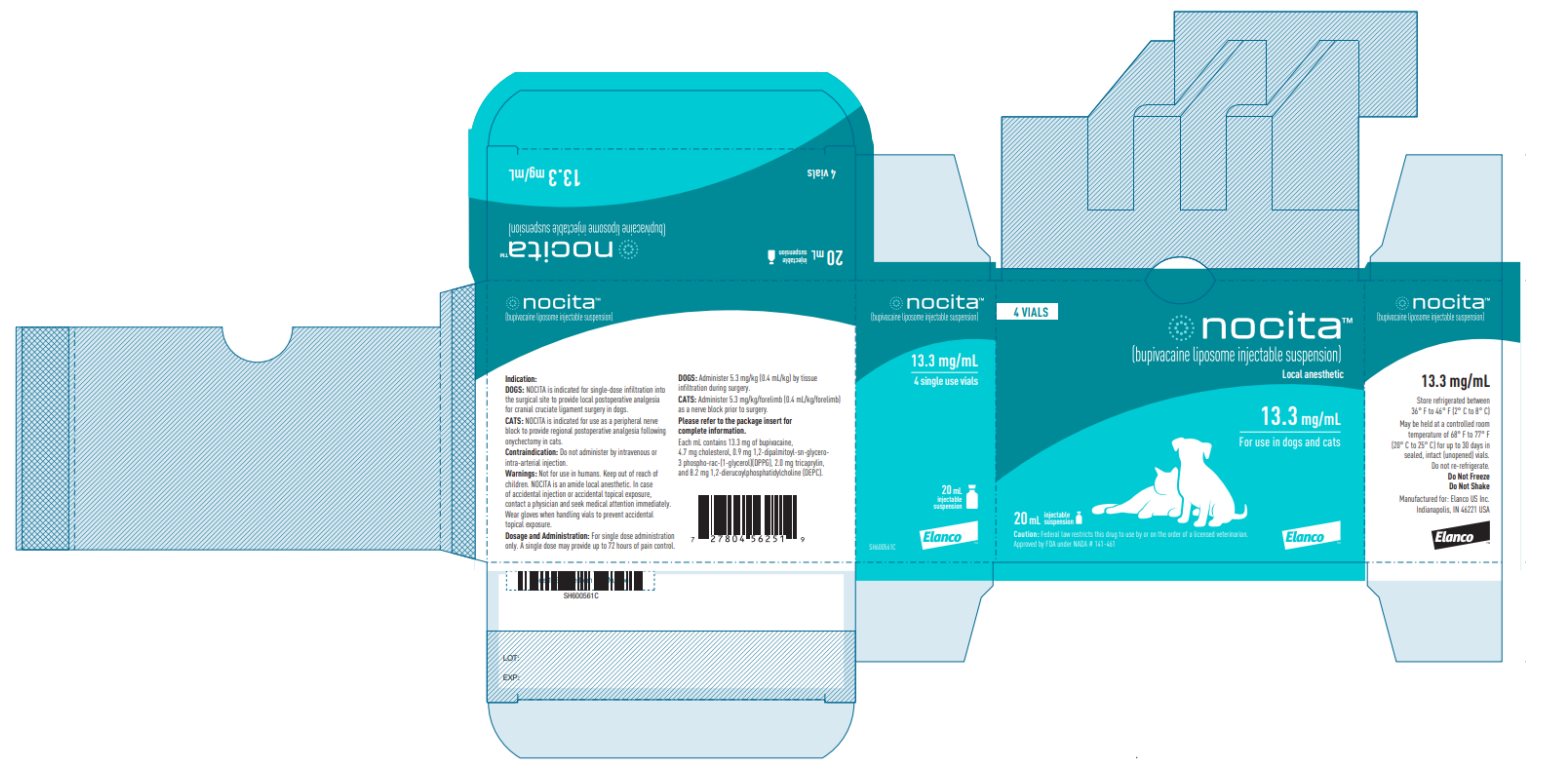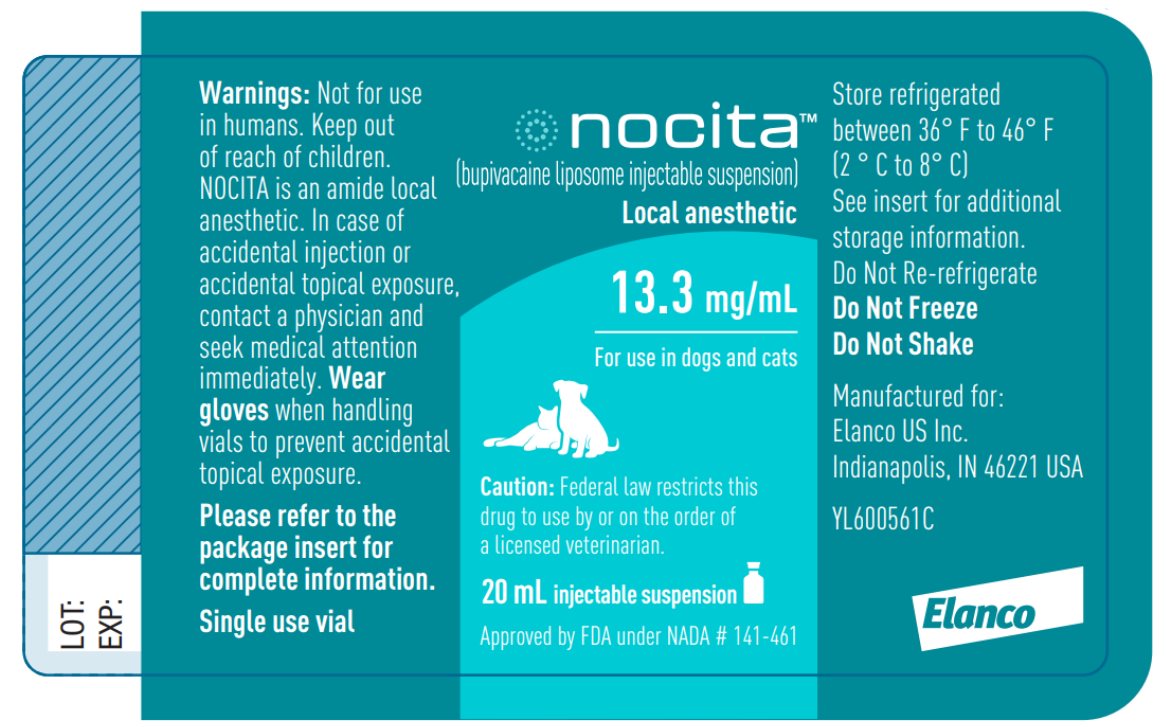 DRUG LABEL: NOCITA
NDC: 58198-5531 | Form: INJECTION, SUSPENSION
Manufacturer: Elanco US Inc.
Category: animal | Type: PRESCRIPTION ANIMAL DRUG LABEL
Date: 20250806

ACTIVE INGREDIENTS: BUPIVACAINE 13.3 mg/1 mL

nocita™

(bupivacaine liposome injectable suspension)

13.3 mg/mL

For local infiltration injection in dogs only

Local Anesthetic

Single use vial

Caution:

Federal law restricts this drug to use by or on the order of a licensed veterinarian.

Description:

NOCITA (bupivacaine liposome injectable suspension) is a sterile, non-pyrogenic, white to off-white, preservative-free, aqueous suspension of multivesicular lipid-based particles containing bupivacaine. Each milliliter of NOCITA contains 13.3 mg of bupivacaine. Inactive ingredients and their nominal concentrations are: cholesterol, 4.7 mg/mL; 1,2-dipalmitoyl-sn-glycero-3 phospho-rac-(1-glycerol) (DPPG), 0.9 mg/mL; tricaprylin, 2.0 mg/mL; and 1,2 dierucocylphosphatidylcholine (DEPC), 8.2 mg/mL. Bupivacaine is related chemically and pharmacologically to the amide-type local anesthetics. Chemically, bupivacaine is 1-butyl-N-(2, 6-dimethylphenyl)-2-piperidinecarboxamide with a molecular weight of 288.4. Bupivacaine structural formula is shown in the illustration to the right.

Indication:

For single-dose infiltration into the surgical site to provide local postoperative analgesia for cranial cruciate ligament surgery in dogs.

Dosage and Administration:

NOCITA is for single dose administration only. A dose of 5.3 mg/kg (0.4 mL/kg) is administered by infiltration injection into the tissue layers at the time of incisional closure. A single dose administered during surgical closure may provide up to 72 hours of pain control.

Dosing Instructions:

- Wear gloves when handling and administering NOCITA (see WARNINGS).
- NOCITA should not be allowed to come into contact with topical antiseptics. When a topical antiseptic such as povidone iodine or chlorhexidine is applied, the area should be allowed to dry before NOCITA is administered into the surgical site.
- Do not shake vial. Invert the vial multiple times to re-suspend the particles immediately prior to withdrawal of the product from the vial.
- Do not puncture the vial multiple times. Puncture the vial stopper once with a single 25 gauge or larger needle. Use aseptic technique to sequentially attach and fill sterile syringes for dosing. Each syringe should be prepared for single patient use only. Discard the vial after all doses are withdrawn.
- Following withdrawal from the vial into a syringe, NOCITA may be stored at controlled room temperature of 68° F to 77° F (20° C to 25° C) for up to 4 hours. Because the formulation does not contain preservative, the syringe(s) must be discarded after 4 hours.
- If the dose volume of NOCITA (0.4 mL/kg) is not sufficient to cover the surgical site, add up to an equal volume of normal (0.9%) sterile saline or Lactated Ringer’s solution. If saline or Lactated Ringer’s is added to the NOCITA dose, administer the entire volume by tissue infiltration into the surgical site. Do not mix with water or other hypotonic solutions as it will result in disruption of the liposomal particles (see CLINICAL PHARMACOLOGY).
  Do not mix NOCITA with other local anesthetics or other drugs prior to administration (see PRECAUTIONS).
- Use a 25 gauge or larger bore needle for administration.
- Administer by infiltration injection: Inject slowly into the tissues using an infiltration injection technique. To obtain adequate coverage, infiltrate all of the tissues in each surgical closure layer. Aspirate frequently to prevent intravascular administration (see CONTRAINDICATIONS).

Contraindications:

Do not administer by intravenous or intra-arterial injection. If accidental intravascular administration occurs, monitor for cardiovascular (dysrhythmias, hypotension, hypertension) and neurologic (tremors, ataxia, seizures) adverse reactions.

Do not use for intra-articular injection. In humans, local anesthetics administered into a joint may cause chondrolysis.

Warnings:

Not for use in humans. Keep out of reach of children.

NOCITA is an amide local anesthetic. In case of accidental injection or accidental topical exposure, contact a physician and seek medical attention immediately.

Wear gloves when handling vials to prevent accidental topical exposure.

Precautions:

Do not administer concurrently with bupivacaine HCl, lidocaine or other amide local anesthetics. A safe interval from time of bupivacaine HCl, lidocaine or other amide local anesthetic administration to time of NOCITA administration has not been determined. The toxic effects of these drugs are additive and their administration should be used with caution including monitoring for neurologic and cardiovascular effects related to toxicity.

The safe use of NOCITA in dogs with cardiac disease has not been evaluated.

The safe use of NOCITA in dogs with hepatic or renal impairment has not been evaluated. NOCITA is metabolized by the liver and excreted by the kidneys.

The ability of NOCITA to achieve effective anesthesia has not been studied. Therefore, NOCITA is not indicated for pre-incisional or pre-procedural loco-regional anesthetic techniques that require deep and complete sensory block in the area of administration.

The safe use of NOCITA for surgical procedures other than cranial cruciate ligament surgery has not been evaluated (see ANIMAL SAFETY and ADVERSE REACTIONS).

The safe use of NOCITA has not been evaluated in dogs younger than 5 months old.

The safe use of NOCITA has not been evaluated in dogs that are pregnant, lactating, or intended for breeding.

Adverse Reactions:

Safety was evaluated in 123 NOCITA treated dogs and 59 saline (placebo) treated dogs in a field study in dogs that underwent cranial cruciate ligament stabilization surgery. Dogs enrolled in the study were 1-13 years of age, and weighed 3.4 to 61.3 kg. NOCITA was administered by infiltrative injection at the surgical site at a dose of 5.3 mg/kg (0.4 mL/kg).

Table D-1. Adverse Reactions Reported During the Study in the Safety Population (any dog that received treatment)

Adverse Reaction | NOCITA (n = 123) | Saline (n = 59)
Discharge from the Incision | 4 (3.3%) | 0 (0.0%)
Incisional Inflammation (erythema and/or edema) | 3 (2.4%) | 0 (0.0%)
Vomiting | 3 (2.4%) | 0 (0.0%)
Abnormalities on Urinalysis (isosthenuria ± proteinuria) | 2 (1.6%) | 0 (0.0%)
Increased ALP | 2 (1.6%) | 0 (0.0%)
Surgical Limb Edema ± Erythema | 1 (0.8%) | 3 (5.1%)
Soft Stool/Diarrhea | 1 (0.8%) | 1 (1.7%)
Inappetence | 1 (0.8%) | 1 (1.7%)
Fever | 1 (0.8%) | 0 (0.0%)
Note: If an animal experienced the same event more than once, only the first occurrence was tabulated.

Contact Information:

To report suspected adverse events, for technical assistance or to obtain a copy of the Safety Data Sheet (SDS), contact Elanco US Inc. at 1-888-545-5973.

For additional information about adverse drug experience reporting for animal drugs, contact FDA at 1-888-FDA-VETS or http://www.fda.gov/reportanimalae

Clinical Pharmacology:

Bupivacaine is an amide, non-opioid local anesthetic. It provides local analgesia by deactivating sodium channels on the nerve membrane, preventing the generation and propagation of nerve impulses. It is only present in small concentrations as uncharged molecules at tissue pH as it is a base with pKa of 8. This un-ionized form provides a lipophilicity that permits the drug to traverse across the nerve cell membrane and upon entering the cell, binds to the intracellular portion of voltage-gated sodium channels and blocks sodium influx into nerve cells, which prevents depolarization. Without depolarization, no initiation or conduction of a pain signal can occur.

Lipid Formulation

Liposomal encapsulation or incorporation in a lipid complex can substantially affect a drug’s functional properties relative to those of the unencapsulated or nonlipid-associated drug. In addition, different liposomal or lipid-complexed products with a common active ingredient may vary from one another in the chemical composition and physical form of the lipid component. Such differences may affect functional properties of these drug products. Do not substitute with other bupivacaine formulations.

After injection of NOCITA into the soft tissue, bupivacaine is released from the multivesicular liposomes over a period of time.

Pharmacokinetics

The pharmacokinetic characterization associated with bupivacaine after subcutaneous NOCITA (bupivacaine liposome injectable suspension) or bupivacaine HCl solution administered to Beagle dogs is provided in Table D-2.

Table D-2. Mean (± SD) Plasma Pharmacokinetic Parameters for bupivacaine after single subcutaneous administration of NOCITA and bupivacaine HCl solution in male and female Beagle dogs in a laboratory study

PK Parameter | NOCITAa 9 mg/kg | NOCITAa 18 mg/kg | NOCITAa 30 mg/kg | bupivacaine HCl 9 mg/kg
N, sex | 6, (3M/3F) | 6, (3M/3F) | 6, (3M/3F) | 6, (3M/3F)
Tmaxb (hr) | 0.5 (0.5-0.5) | 0.5 (0.5-0.5) | 60.0 (0.5-72) | 0.5 (0.5-0.5)
Cmax (ng/mL) | 488 (335) | 560 (299) | 633 (280) | 1420 (355)
AUC(0-72) (ng*hr/mL) | 9100 (4460) | 12800 (2020) | 25600 (8160) | 9720 (1860)
T1/2c (hr) | 36.2 (12.4) | 25.7 (8.15) | 43.9 (12.5) | 10.1 (8.54)
a 5.3 mg/kg NOCITA bupivacaine base is equal to 6 mg/kg bupivacaine HCl. NOCITA doses in this table are in the bupivacaine HCl equivalent.
b Median (Range)
c Reported from steady state concentrations

Following a single subcutaneous dose of 9 mg/kg and 18 mg/kg NOCITA, median time to reach Cmax was rapid (0.5 hr) but it was delayed significantly at a high dose of 30 mg/kg (60 hr). Following equivalent doses (9 mg/kg) of NOCITA and bupivacaine HCl solution, the mean bupivacaine AUC(0-72) and Tmax were comparable. However, due to the slow release mechanism of the NOCITA formulation, the mean Cmax and T½ were approximately 3-fold lower and 3.5-fold higher, respectively. Following an increase in dose of NOCITA, the bupivacaine pharmacokinetics was nonlinear with high variability in exposure parameters. Both Cmax and AUC(0-72) increase with dose but the increases were less than dose proportional. Further, the non-linear bupivacaine pharmacokinetics was made evident by an increase in the terminal phase half-life with the increase in dose.

Effectiveness:

Effectiveness was demonstrated in a multi-center, placebo-controlled, randomized and masked field study in client-owned dogs undergoing cranial cruciate ligament stabilization surgery. In this study, 182 dogs were enrolled in the study and randomized to treatment with NOCITA (n = 123) or saline (placebo, n = 59). The per protocol population for effectiveness was 112 NOCITA treated dogs and 52 saline dogs.

Dogs received an opioid analgesic just prior to general anesthesia and surgery. Surgical repair technique was at the discretion of the surgeon, and included extra-capsular repair, tibial plateau leveling osteotomy (TPLO), or tibial tuberosity advancement (TTA).

Table D-3 shows the number and percent of surgical procedures by treatment group.

Table D-3. Surgical Procedure by Treatment Group

Surgical Procedure | NOCITA (n = 112) n (%) | Saline (n = 52) n (%) | Total (n = 164) n (%)
Extra-capsular repair | 52 (46.4) | 24 (46.2) | 76 (46.3)
TPLO | 50 (44.6) | 22 (42.3) | 72 (43.9)
TTA | 10 (8.9) | 6 (11.5) | 16 (9.8)

Using an infiltration injection technique, a single dose of NOCITA or saline was infiltrated into the tissue layers during surgical closure. NOCITA or saline was administered either as is or with the addition of up to an equal volume of sterile saline. Pain was assessed by trained observers using the Glasgow Composite Measure Pain Scale-Short Form (CMPS-SF) for up to 72 hours following surgical closure. Pain assessments were conducted prior to surgery, and at 0.5, 1, 2, 4, 8, 12, 24, 30, 36, 48, 56 and 72 hours post-surgery. Dogs with a CMPS-SF score ≥ 6 or were determined to be painful by the investigator received rescue analgesic medication and were classified as treatment failures. No further CMPS-SF pain assessments were recorded for dogs that received rescue analgesic medication. The primary variable for effectiveness was evaluated over the first 24-hour time interval. The percent of treatment success for NOCITA was significantly different from and greater than saline at the first 24-hour time interval (p = 0.0322). The 24-48 hour and 48-72 hour time intervals were evaluated as secondary variables and support effective use of NOCITA for up to 72 hours of analgesia.

Table D-4. Number and Percent Effectiveness for NOCITA and Saline (Placebo) at each Time Interval*

Time Interval for Pain Evaluation | NOCITA (n = 112) | Saline (n = 52)
0-24 hours | 77 (68.8%) | 19 (36.5%)
24-48 hours | 72 (64.3%) | 18 (34.6%)
48-72 hours | 69 (61.6%) | 17 (32.7%)
*For dogs that were deemed treatment failures over any time interval, the failure was carried forward to all subsequent time intervals. Therefore, the time intervals for evaluating treatment success are equivalent to 0-24 hours, 0-48 hours, and 0-72 hours.

Animal Safety:

In a 4-week laboratory study with a 4-week recovery period, 60 healthy dogs aged 5-6 months were administered NOCITA at 8, 16 and 26.6 mg/kg. These doses correspond to 1.5, 3 and 5 times the maximum labeled dose of 5.3 mg/kg bupivacaine base. The active control group was administered 9 mg/kg bupivacaine HCl (equivalent to 8 mg/kg bupivacaine base), and the placebo group was administered 1.2 mL/kg saline. All dogs were dosed by subcutaneous injection twice weekly for 4 weeks. Doses alternated between two injection sites to the right or left of dorsal midline near the scapula. There were 6 dogs/sex/group for the first 4 weeks, and then 3 dogs/sex/group were maintained and monitored during a 4-week recovery period.

All dogs survived the study, and there were no clinically relevant treatment-related effects on clinical observations, physical examination, body weight, electrocardiograms (ECG), hematology, serum chemistry, urinalysis, coagulation, and organ weights. Injection site reactions on histopathology included minimal to moderate edema, granulomatous inflammation and mineralization in the subcutaneous tissue in some dogs that received NOCITA. In dogs that were evaluated immediately after the 4-week treatment period, granulomatous inflammation was characterized by numerous vacuolated macrophages and fewer lymphocytes, plasma cells and/or multinucleated giant cells. The inflammation was often associated with mineralization and/or edema. In the dogs that were maintained for the 4-week recovery period, there were fewer dogs with granulomatous inflammation and mineralization at the injection sites. The inflammation was characterized by a greater number of giant cells. One 9 mg/kg NOCITA group male dog had minimal subcutaneous edema that was not associated with cellular inflammation. These inflammatory changes are associated with administration of the liposomal suspension, and did not occur in the saline and bupivacaine HCl groups.

Storage Conditions:

Unopened vials should be stored refrigerated between 36° F to 46° F (2° C to 8° C)

NOCITA may be held at a controlled room temperature of 68° F to 77° F (20° C to 25° C) for up to 30 days in sealed, intact (unopened) vials. Do not re-refrigerate. Do Not Freeze.

How Supplied:

13.3 mg/mL bupivacaine liposome injectable suspension in 10 mL or 20 mL single use vial.

10 mL supplied in 4-vial carton. 20 mL supplied in a single vial carton and 4-vial carton.

Approved by FDA under NADA # 141-461

Manufactured for:
Elanco US Inc.
Indianapolis, IN 46221 USA

Nocita, Elanco and the diagonal bar logo are trademarks of Elanco or its affiliates.
© 2025 Elanco or its affiliates

Rev. date 05/2025

PA600561X

ElancoTM

nocita™

(bupivacaine liposome injectable suspension)

13.3 mg/mL

For use as a peripheral nerve block in cats only

Local Anesthetic

Single use vial

Caution:

Federal law restricts this drug to use by or on the order of a licensed veterinarian.

Description:

NOCITA (bupivacaine liposome injectable suspension) is a sterile, non-pyrogenic white to off-white, preservative-free, aqueous suspension of multivesicular lipid-based particles containing bupivacaine. Each milliliter of NOCITA contains 13.3 mg/mL of bupivacaine. Inactive ingredients and their nominal concentrations are: cholesterol, 4.7 mg/mL; 1,2-dipalmitoyl-sn-glycero-3 phospho-rac-(1-glycerol) (DPPG), 0.9 mg/mL; tricaprylin, 2.0 mg/mL; and 1,2 dierucocylphosphatidylcholine (DEPC), 8.2 mg/mL. Bupivacaine is related chemically and pharmacologically to the amide-type local anesthetics. Chemically, bupivacaine is 1-butyl-N-(2, 6-dimethylphenyl)-2-piperidinecarboxamide with a molecular weight of 288.4.
Bupivacaine structural formula is shown in the illustration to the right.

Indication:

For use as a peripheral nerve block to provide regional postoperative analgesia following onychectomy in cats.

Dosage and Administration:

NOCITA is for administration only once prior to surgery. Administer 5.3 mg/kg per forelimb (0.4 mL/kg per forelimb, for a total dose of 10.6 mg/kg/cat) as a 4-point nerve block (described below) prior to onychectomy.
Administration prior to surgery may provide up to 72 hours of pain control.

Prepare Dose(s):

- Wear gloves when handling and administering NOCITA (see WARNINGS).
- NOCITA should not be allowed to come into contact with topical antiseptics. When a topical antiseptic such as povidone iodine or chlorhexidine is applied, the area should be allowed to dry before NOCITA is administered.
- Do not shake vial. Invert the vial multiple times to re-suspend the particles immediately prior to withdrawal of the product from the vial.
- Do not puncture the vial multiple times. Puncture the vial stopper once with a single 25 gauge or larger needle. Use aseptic technique to sequentially attach and fill sterile syringes. Each syringe should be prepared for single patient use only. Discard the vial after all doses are withdrawn.
- Following withdrawal from the vial into a syringe, NOCITA may be stored at controlled room temperature of 68° F to 77° F (20° C to 25° C) for up to 4 hours. Because the formulation does not contain preservative, the syringe(s) must be discarded after 4 hours.
- Do not dilute NOCITA prior to use as a nerve block in cats.
  Do not mix with water or other hypotonic solutions as it will result in disruption of the liposomal particles (see CLINICAL PHARMACOLOGY).
  Do not mix NOCITA with other local anesthetics or other drugs prior to administration (see PRECAUTIONS).
- Use a 25 gauge or larger bore needle for administration.

Dose Administration:

- Aspirate prior to injecting to prevent intravascular administration (see CONTRAINDICATIONS).

Table C-1. Dose Administration for One Forelimb.^1

Legend |  |  | Abbreviations
Needle insertion point | Needle withdrawal + drug injection |  |  | SpU - Styloid process of the ulna
Needle advancement; Drug injection point | Needle redirection to a 90˚ angle to the palmar plane |  |  | ACb - Accessory carpal bone
Dose Volume per Injection (% of total 0.4 mL/kg/forelimb volume) and Description
A. 0.14 mL/kg (35%) Superficial Branch of the Radial Nerve: At the center of the limb, on the dorsal aspect at the level of the antebrachiocarpal joint, insert the needle subcutaneously with the bevel up (•). Advance the needle subcutaneously as depicted by the dotted line and arrow and inject (ο) adjacent to the confluence of the accessory cephalic and cephalic veins.; Dorsal |  | B. 0.08 mL/kg (20%) Dorsal Branch of the Ulnar Nerve: Palpate a groove between the accessory carpal bone (ACb, in the base of the carpal pad) and the styloid process of the ulna (SpU). Distal to this groove, insert the needle subcutaneously with the bevel up and advance the needle proximally. Inject once the tip reaches the midpoint of the groove.; Lateral
C. 0.16 mL/kg (40%) Median Nerve and Superficial Branch of the Palmar Branch of the Ulnar Nerve: Insert the needle subcutaneously with the bevel up lateral to the distal tip of the accessory carpal pad and advance the needle medially 2/3 the width of the limb, until the tip is located near the base of the first digit. Inject 2/3 of the volume at this point and the remaining volume while withdrawing the needle (solid grey arrow). Gently massage for 5 seconds.; Palmar |  | D. 0.02 mL/kg (5%) Deep Branch of the Palmar Branch of the Ulnar Nerve: Orient the needle perpendicular to the long axis of the limb at the level of the ACb. Insert the needle subcutaneously and advance the needle laterally until it contacts the medial aspect of the ACb. Redirect the needle dorsally by rotating the needle 90°, advance it along the medial side of the ACb 2-3 mm until it penetrates the flexor retinaculum, and inject.; Palmar

Contraindications:

Do not administer by intravenous or intra-arterial injection. If accidental intravascular administration occurs, monitor for cardiovascular (dysrhythmias, hypotension, hypertension) and neurologic (tremors, ataxia, seizures) adverse reactions.

Do not use for intra-articular injection. In humans, local anesthetics administered into a joint may cause chondrolysis.

Warnings:

Not for use in humans. Keep out of reach of children.

NOCITA is an amide local anesthetic. In case of accidental injection or accidental topical exposure, contact a physician and seek medical attention immediately.

Wear gloves when handling vials to prevent accidental topical exposure.

Precautions:

Do not administer concurrently with bupivacaine HCl, lidocaine or other amide local anesthetics. A safe interval from time of bupivacaine HCl, lidocaine or other amide local anesthetic administration to time of NOCITA administration has not been determined. The toxic effects of these drugs are additive and their administration should be used with caution including monitoring for neurologic and cardiovascular effects related to toxicity.

The safe use of NOCITA in cats with cardiac disease has not been evaluated.

The safe use of NOCITA in cats with hepatic or renal impairment has not been evaluated. NOCITA is metabolized by the liver and excreted by the kidneys.

The ability of NOCITA to achieve effective anesthesia has not been evaluated.

The safe use of NOCITA in cats for surgical procedures other than onychectomy has not been evaluated.

The safe use of NOCITA has not been evaluated in cats younger than 5 months old.

The safe use of NOCITA has not been evaluated in cats that are pregnant, lactating, or intended for breeding.

Adverse Reactions:

Safety was evaluated in 120 NOCITA treated cats and 121 saline (placebo) treated cats in a field study in cats undergoing onychectomy. Cats enrolled in the study were 5 months to 10 years of age, and weighed 2.0 to 9.3 kg. NOCITA was administered as a 4-point peripheral nerve block at a dose of 5.3 mg/kg per forelimb (0.4 mL/kg per forelimb).

Table C-2: Adverse Reactions Reported During the Study in the Safety Population (any cat that received treatment)

Adverse Reaction | NOCITA (n = 120) | Saline (n = 121)
Elevated body temperature* | 8 (6.7%) | 5 (4.1%)
Surgical site infection | 4 (3.3%) | 1 (0.8%)
Chewing/licking of surgical site | 3 (2.5%) | 2 (1.7%)
Diarrhea | 2 (1.7%) | 1 (0.8%)
Injection site erythema | 1 (0.8%) | 0 (0.0%)
Swelling of paw; erythematous digits | 1 (0.8%) | 0 (0.0%)
Note: If an animal experienced the same event more than once, only the first occurrence was tabulated.
* Elevated body temperature was defined as temperature ≥ 103° F on Day 3 and normal before surgery. One of the NOCITA treated cats had an infection of one surgical site. No other cat with elevated body temperature showed evidence of infection or illness.

Eight cats, 4 in each group, had normal platelet counts before treatment on Day 0 and platelet counts below the reference range (155,000-641,000/μL) on Day 3. The 4 cats treated with NOCITA had platelet counts of 42,000 to 100,000/μL, and the 4 cats in the saline group had platelet counts of 114,000 to 149,000/μL. Decreased platelet counts were not associated with clinical signs.

In a pilot study with 62 cats undergoing onychectomy (31 cats treated with NOCITA and 31 with saline), one NOCITA treated cat had a motor deficit (unilateral knuckling) which resolved by the next morning following surgery. Another NOCITA treated cat had bruising at the injection sites.

Contact Information:

To report suspected adverse events, for technical assistance or to obtain a copy of the Safety Data Sheet (SDS), contact Elanco US Inc. at 1-888-545-5973.

For additional information about adverse drug experience reporting for animal drugs, contact FDA at 1-888-FDA-VETS or http://www.fda.gov/reportanimalae

Clinical Pharmacology:

Bupivacaine is an amide, non-opioid local anesthetic. It provides local analgesia by deactivating sodium channels on the nerve membrane, preventing the generation and propagation of nerve impulses. It is only present in small concentrations as uncharged molecules at tissue pH as it is a base with pKa of 8. This un-ionized form provides a lipophilicity that permits the drug to traverse across the nerve cell membrane and upon entering the cell, binds to the intracellular portion of voltage-gated sodium channels and blocks sodium influx into nerve cells, which prevents depolarization. Without depolarization, no initiation or conduction of a pain signal can occur.

Lipid Formulation

Liposomal encapsulation or incorporation in a lipid complex can substantially affect a drug's functional properties relative to those of the unencapsulated or nonlipid-associated drug. In addition, different liposomal or lipid-complexed products with a common active ingredient may vary from one another in the chemical composition and physical form of the lipid component. Such differences may affect functional properties of these drug products. Do not substitute with other bupivacaine formulations.

After injection of NOCITA, bupivacaine is released from the multivesicular liposomes over a period of time.

Pharmacokinetics

The pharmacokinetic characterization associated with bupivacaine after subcutaneous NOCITA (bupivacaine liposome injectable suspension) or bupivacaine HCl solution administered to cats evaluated for 168 hours is provided in Table C-3.

Table C-3. Plasma pharmacokinetic parameters for bupivacaine after single subcutaneous administration of NOCITA and bupivacaine HCl solution in male and female cats in a laboratory study.

PK Parameter | NOCITAa 3 mg/kg | NOCITAa 9 mg/kg | NOCITAa 15 mg/kg | bupivacaine HCl 1 mg/kg
N | 6 | 6 | 6 | 6
Tmaxb (hr) | 12.5 (1-48) | 10 (1-24) | 1.5 (1-24) | 1 (1-4)
Tlastb(hr) | 108 (72-144) | 120 (72-168) | 144 (120-168) | 18 (12-24)
Cmaxc (ng/mL) | 311.4 (82.2-565) | 620.2 (374-892) | 709.7 (462-1090) | 263.9 (60.5-506)
AUC(last)c (ng*hr/mL) | 11347 (5176-15767) | 32561 (19390-47532) | 38475 (26460-48252) | 1608 (314-2363)
a 5.3 mg/kg NOCITA bupivacaine base is equal to 6 mg/kg bupivacaine HCl. NOCITA doses in this table are in the bupivacaine HCl equivalent.
b Median (range)
c Mean (range)
Tmax = time to maximum plasma concentration
Tlast = time to last quantifiable plasma concentration
Cmax = maximum plasma concentration
AUClast = area under the curve from the time of dosing to the last quantifiable plasma concentration

Following a single subcutaneous dose of NOCITA, there was a less than dose proportional increase in Cmax and AUClast across the dose range tested (3-15 mg/kg). There was a high variability in all reported parameters. Half-life is not reported for NOCITA in cats because the prolonged absorption confounds the estimation of the terminal elimination phase. Therefore, Tlast is included as a more appropriate measure of the duration of quantifiable plasma concentrations.

Effectiveness:

Effectiveness was demonstrated in a multi-center, placebo-controlled, randomized and masked field study in client-owned cats undergoing bilateral forelimb onychectomy. In this study, 241 cats were enrolled in the study and randomized to treatment with NOCITA (n = 120) or saline (placebo, n = 121).

Cats received an opioid analgesic just prior to general anesthesia and surgery. The nerve block injection sites were shaved and a standard surgical preparation with chlorhexidine or povidone iodine was used. Prior to onychectomy, NOCITA or saline was administered as a 4-point nerve block (see DOSING INSTRUCTIONS).

Pain was assessed by trained observers using a modified version of the UNESP-Botucatu Multidimensional Composite Pain Scale for up to 72 hours following extubation. Pain assessments were conducted prior to surgery, and at 0.5, 1, 2, 4, 8, 12, 24, 30, 36, 48, 56 and 72 hours post-surgery. Cats with a composite pain score ≥ 6 or that were determined to be painful by the assessor received rescue analgesic medication and were classified as treatment failures. After receiving rescue analgesia, cats did not have further pain assessments performed. The primary variable for effectiveness was evaluated over the first 24-hour time interval. The percent of treatment success for NOCITA was significantly greater than saline for the 0-24 hour time interval (p = 0.0252). The 0-48 hour and 0-72 hour time intervals were evaluated as secondary variables and support effective use of NOCITA for up to 72 hours of analgesia.

Table C-4. Number and Percent Effectiveness for NOCITA and Saline (Placebo) Groups at each Time Interval

Time Interval for Pain Evaluation | NOCITA | Saline
0-24 hours | 88/117 (75.2%) | 48/119 (40.3%)
0-48 hours | 79/115 (68.7%) | 41/118 (34.7%)
0-72 hours | 78/114 (68.4%) | 42/119 (35.3%)

The per protocol populations for effectiveness varied for each pain assessment time interval because of protocol deviations affecting only one of the three time intervals for some cats.

Animal Safety:

In a 22 day laboratory study, 40 healthy cats (4 cats/sex/group) aged 5-6 months were administered negative control (2.37 mL/kg saline), active control (5.3 mg/kg bupivacaine HCl), or NOCITA at 10.6, 21.2, or 31.8 mg/kg via injection using a suprainguinal approach for a femoral nerve block of the right hindlimb on Days 0, 9 and 18. These NOCITA doses correspond to 1, 2 and 3 times the maximum labeled total dose of 10.6 mg/kg/cat (representing 2, 4 and 6 times the maximum labeled dose of 5.3 mg/kg/forelimb).

Two cats died during the study. One male in the active control group died during recovery from anesthesia after the second dose and no definitive cause of death was determined. One female in the 31.8 mg/kg group was euthanized on Day 15. This cat developed a suppurative, open, necrotic wound over the region of the right stifle after the second dose administration.

For the cats who survived the study, there were no clinically relevant treatment-related effects on electrocardiograms, hematology, serum chemistry, urinalysis, coagulation, and organ weights. Right hindlimb impairment was expected because the entire dose was administered as a femoral nerve block. Right hindlimb impairment occurred in 23 of the 24 NOCITA cats which persisted for 1-5 days; 2 negative control cats which persisted for 1 day; and none of the active control cats. Left hindlimb impairment was observed the day after the first dose in one cat in the 21.2 mg/kg group. NOCITA treatment-related findings were observed on histopathology of soft tissue and the femoral nerve at the injection sites. Injection site soft tissue histopathology findings included subacute or chronic inflammation, mineralization, myofiber degeneration and myofiber necrosis. Injection site femoral nerve histopathology findings included subacute or chronic inflammation.

Sporadic clinical observations and histopathology findings throughout both negative and active control groups and NOCITA groups included: soft or watery or mucoid stool; inguinal swelling on the right hindlimb noted after only the first dose; abrasions or scabbing noted at the right abdominal and inguinal regions as well as on the right hindlimb and at the right stifle; histopathology findings at or near the injection site or right stifle included ulceration and suppurative crusts on the skin, histopathology findings at the injection site of subcutaneous foreign material and fibrosis, and myofiber regeneration.

Storage Conditions:

Unopened vials should be stored refrigerated between 36° F to 46° F (2° C to 8° C)

NOCITA may be held at a controlled room temperature of 68° F to 77° F (20° C to 25° C) for up to 30 days in sealed, intact (unopened) vials. Do not re-refrigerate. Do Not Freeze.

How Supplied:

13.3 mg/mL bupivacaine liposome injectable suspension in 10 mL or 20 mL single use vial.

10 mL supplied in 4-vial carton. 20 mL supplied in a single vial carton and 4-vial carton.

Approved by FDA under NADA # 141-461

Manufactured for: Elanco US Inc., Indianapolis, IN 46221 USA

Nocita, Elanco and the diagonal bar logo are trademarks of Elanco or its affiliates.

Rev. date 05/2025

REFERENCES

Reference:

1. Location and relative volumes based on: Enomoto M, Lascelles BDX and Gerard MP. Defining the local nerve blocks for feline distal thoracic limb surgery: a cadaveric study. Journal of Feline Medicine and Surgery. 2016 18 (10): 838-845.

PA600561X

ElancoTM

Principal Display Panel - 10 mL Carton Label

4 VIALS

nocita™
(bupivacaine liposome injectable suspension)

Local anesthetic

13.3 mg/mL

For use in dogs and cats

10 mL
injectable
suspension

Caution: Federal law restricts this drug to use by or on the order of a licensed veterinarian.

Approved by FDA under NADA # 141-461

ElancoTM

Principal Display Panel - 10 mL Vial Label

nocita™
(bupivacaine liposome injectable suspension)

Local anesthetic

13.3 mg/mL

For use in dogs and cats

Approved by FDA under NADA # 141-461

Warnings: Not for use
in humans. Keep out of
reach of children.

See package insert
for complete product
information.

Single use vial

10 mL
injectable
suspension

Principal Display Panel - 20 mL Carton Label

1 VIAL

nocita™
(bupivacaine liposome injectable suspension)

Local anesthetic

13.3 mg/mL

For use in dogs and cats

20 mL
injectable
suspension

Caution: Federal law restricts
this drug to use by or on the order
of a licensed veterinarian.

Approved by FDA under NADA # 141-461

ElancoTM

4 VIALS

nocita™
(bupivacaine liposome injectable suspension)

Local anesthetic

13.3 mg/mL

For use in dogs and cats

20 mL
injectable
suspension

Caution: Federal law restricts this drug to use by or on the order of a licensed veterinarian.

Approved by FDA under NADA # 141-461

ElancoTM

Principal Display Panel - 20 mL Vial Label

nocita™
(bupivacaine liposome injectable suspension)

Local anesthetic

13.3 mg/mL

For use in dogs and cats

Caution: Federal law restricts this
drug to use by or on the order of
a licensed veterinarian.

20 mL injectable suspension

Approved by FDA under NADA # 141-461

Warnings: Not for use
in humans. Keep out
of reach of children.
NOCITA is an amide local
anesthetic. In case of
accidental injection or
accidental topical exposure,
contact a physician and
seek medical attention
immediately. Wear
gloves when handling
vials to prevent accidental
topical exposure.

Please refer to the
package insert for
complete information.

Single use vial